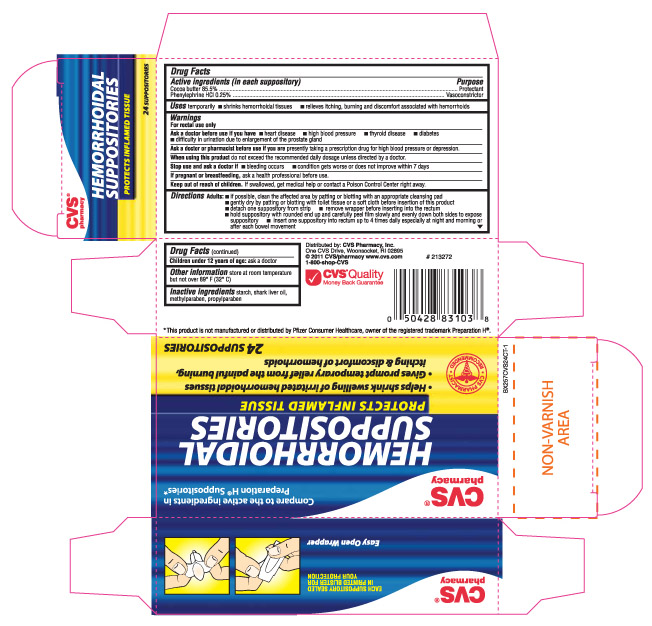 DRUG LABEL: COCOA BUTTER, PHENYLEPHRINE HYDROCHLORIDE
NDC: 59779-401 | Form: SUPPOSITORY
Manufacturer: CVS
Category: otc | Type: HUMAN OTC DRUG LABEL
Date: 20110701

ACTIVE INGREDIENTS: COCOA BUTTER .855 g/1 g; PHENYLEPHRINE HYDROCHLORIDE .0025 g/1 g
INACTIVE INGREDIENTS: SHARK LIVER OIL; STARCH, CORN; METHYLPARABEN; PROPYLPARABEN

drug facts

Active ingredients (in each suppository) Purpose
Cocoa Butter 85.5%........................................................................ Protectant
Phenylephrine HCL 0.25%............................................................... Vasoconstrictor

Active ingredients (in each suppository) Purpose
Cocoa Butter 85.5%........................................................................ Protectant
Phenylephrine HCL 0.25%............................................................... Vasoconstrictor
________________________________________________________________________________________
Uses temporarily - Shrinks hemorrhoidal tissues - relieves itching, burning and discomfort associated with hemorrhoids

Keep out of reach of children. If swallowed, get
medical help or contact a Poison Control Center right away.

INDICATIONS AND USAGE

Uses - shrinks hemorrhoidal tissues - relieves itching, burning and discomfort associated with hemorrhoids

Warnings
For rectal use only
____________________________________________________
Ask a doctor before use if you have - heart disease - high blood pressure
- thyroid disease - diabetes - difficulty in urination due to enlargement of the prostate gland
_____________________________________________________
Ask a doctor or pharmacist before use if you are - presently taking a prescription
drug for high blood pressure or depression
______________________________________________________
Stop use and ask a doctor if
- bleeding occurs - condition gets worse or does not improve within 7 days
______________________________________________________
If pregnant or breastfeeding, ask a health professional before use
_______________________________________________________________
Keep out of reach of children. If swallowed, get
medical help or contact a Poison Control Center
right away
______________________________________________________

Directions
- Adults - if possible, clean the affected area by patting or blotting with an appropriate cleansing pad
- gently dry by patting or blotting with toilet tissue or a soft cloth before insertion of this product
- detach one suppository from strip - remove wrapper before inserting into the rectum - hold suppository
with rounded end up and carefully peel film slowly and evenly down both sides to expose the suppository
- insert one suppository into rectum up to 4 times daily especially at night and morning or after each bowel
movement
Children under 12 years of age: ask a doctor
________________________________________________________________________________________
Other information - store at room temperature but not over 89 degrees F (32 degrees C)

INACTIVE INGREDIENT

Inactive Ingredients starch, shark liver oil, methylparaben, propylparaben